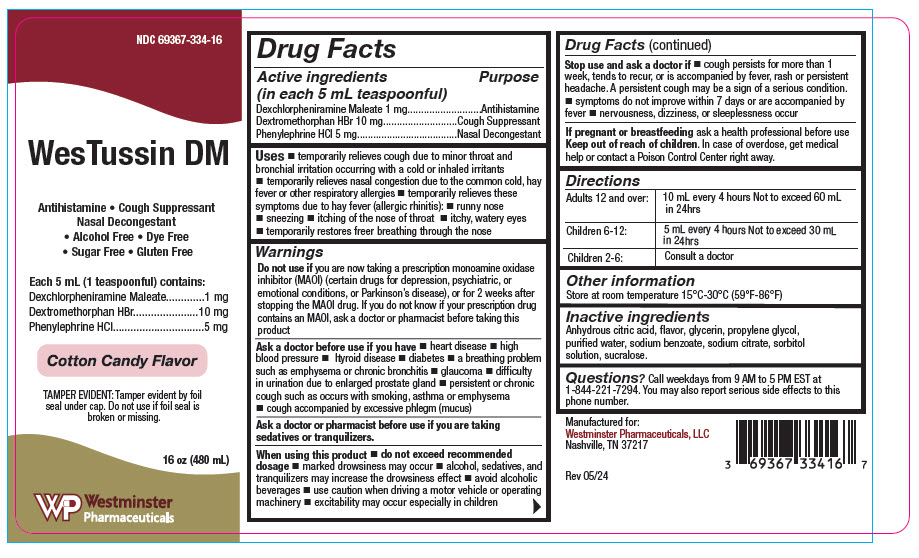 DRUG LABEL: WesTussin DM
NDC: 69367-334 | Form: SYRUP
Manufacturer: Westminster Pharmaceuticals, LLC
Category: otc | Type: HUMAN OTC DRUG LABEL
Date: 20240723

ACTIVE INGREDIENTS: DEXCHLORPHENIRAMINE MALEATE 1 mg/5 mL; DEXTROMETHORPHAN HYDROBROMIDE 10 mg/5 mL; PHENYLEPHRINE HYDROCHLORIDE 5 mg/5 mL
INACTIVE INGREDIENTS: ANHYDROUS CITRIC ACID; GLYCERIN; PROPYLENE GLYCOL; WATER; SODIUM BENZOATE; SODIUM CITRATE, UNSPECIFIED FORM; SORBITOL; SUCRALOSE

WesTussin DM

Drug Facts

ACTIVE INGREDIENT

Active ingredients (in each 5 mL teaspoonful) | Purpose
Dexchlorpheniramine Maleate 1 mg | Antihistamine
Dextromethorphan HBr 10 mg | Cough Suppressant
Phenylephrine HCl 5 mg | Nasal Decongestant

Uses

- temporarily relieves cough due to minor throat and bronchial irritation occurring with a cold or inhaled irritants
- temporarily relieves nasal congestion due to the common cold, hay fever or other respiratory allergies
- temporarily relieves these symptoms due to hay fever (allergic rhinitis):
- runny nose
- sneezing
- itching of the nose of throat
- itchy, watery eyes
- temporarily restores freer breathing through the nose

Warnings

Do not use if you are now taking a prescription monoamine oxidase inhibitor (MAOI) (certain drugs for depression, psychiatric, or emotional conditions, or Parkinson's disease), or for 2 weeks after stopping the MAOI drug. If you do not know if your prescription drug contains an MAOI, ask a doctor or pharmacist before taking this product

Ask a doctor before use if you have

- heart disease
- high blood pressure
- thyroid disease
- diabetes
- a breathing problem such as emphysema or chronic bronchitis
- glaucoma
- difficulty in urination due to enlarged prostate gland
- persistent or chronic cough such as occurs with smoking, asthma or emphysema
- cough accompanied by excessive phlegm (mucus)

Ask a doctor or pharmacist before use if you are taking sedatives or tranquilizers.

When using this product

- do not exceed recommended dosage
- marked drowsiness may occur
- alcohol, sedatives, and tranquilizers may increase the drowsiness effect
- avoid alcoholic beverages
- use caution when driving a motor vehicle or operating machinery
- excitability may occur especially in children

Stop use and ask a doctor if

- cough persists for more than 1 week, tends to recur, or is accompanied by fever, rash or persistent headache. A persistent cough may be a sign of a serious condition.
- symptoms do not improve within 7 days or are accompanied by fever
- nervousness, dizziness, or sleeplessness occur

PREGNANCY OR BREAST FEEDING

If pregnant or breastfeeding ask a health professional before use

Keep out of reach of children. In case of overdose, get medical help or contact a Poison Control Center right away.

Directions

Adults 12 and over: | 10 mL every 4 hours Not to exceed 60 mL in 24hrs
Children 6-12: | 5 mL every 4 hours Not to exceed 30 mL in 24hrs
Children 2-6: | Consult a doctor

Other information

Store at room temperature 15°C-30°C (59°F-86°F)

Inactive ingredients

Citric acid anhydrous, cotton candy flavoring, glycerin, propylene glycol, purified water, sodium benzoate, sodium citrate dihydrate, sorbitol solution, sucralose.

Questions?

Call weekdays from 9 AM to 5 PM EST at 1-844-221-7294. You may also report serious side effects to this phone number.

PRINCIPAL DISPLAY PANEL - 480 mL Bottle Label

NDC 69367-334-16

WesTussin DM

Antihistamine • Cough Suppressant
Nasal Decongestant
• Alcohol Free • Dye Free
• Sugar Free • Gluten Free

Each 5 mL (1 teaspoonful) contains:
Dexchlorpheniramine Maleate
1 mg
Dextromethorphan HBr
10 mg
Phenylephrine HCl
5 mg

Cotton Candy Flavor

TAMPER EVIDENT: Tamper evident by foil
seal under cap. Do not use if foil seal is
broken or missing.

16 oz (480 mL)

Westminster
Pharmaceuticals